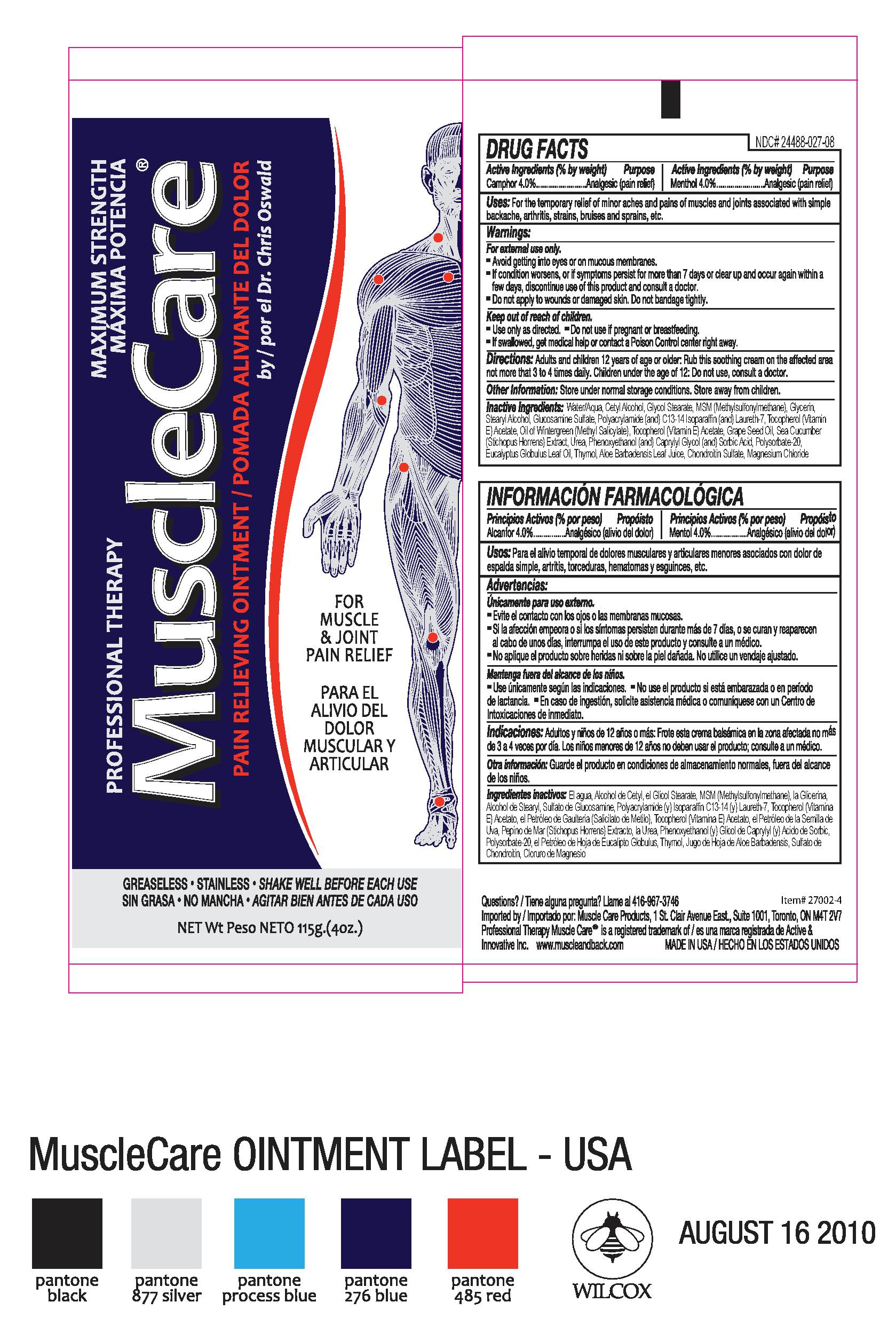 DRUG LABEL: Professional Therapy MuscleCare
NDC: 70039-298 | Form: CREAM
Manufacturer: Active and Innovative Inc.
Category: otc | Type: HUMAN OTC DRUG LABEL
Date: 20160811

ACTIVE INGREDIENTS: CAMPHOR (SYNTHETIC) 40 mg/1 g; MENTHOL 40 mg/1 g
INACTIVE INGREDIENTS: GLYCOL STEARATE; DIMETHYL SULFONE; GLYCERIN; STEARYL ALCOHOL; SORBIC ACID; THYMOL; CHONDROITIN SULFATE (CHICKEN); CETYL ALCOHOL; WATER; GRAPE SEED OIL; CAPRYLYL GLYCOL; POLYACRYLAMIDE (1500 MW); C13-14 ISOPARAFFIN; LAURETH-7; .ALPHA.-TOCOPHEROL ACETATE, DL-; MAGNESIUM CHLORIDE; GLUCOSAMINE SULFATE; METHYL SALICYLATE; STICHOPUS SEA CUCUMBER; (HYDROXYMETHYL)UREA; PHENOXYETHANOL; POLYSORBATE 20; EUCALYPTUS GLOBULUS LEAF; ALOE VERA LEAF

Professional Therapy MuscleCare pain relieving ointment, 4oz

PURPOSE

FOR MUSCLE & JOINT PAIN RELIEF

Active Ingredietns (% by weight) Purpose

Camphor 4%.........................Analgesic (pain relief)

Menthol 4%...........................Analgesic (pain relief)

Uses:

For the temporary relief of minor aches and pains of muscles and joints associated with simple backache, arthritis, strains, bruises and sprains, etc.

Warnings:

For external use only.

- Avoid getting into eyes or on mucous membranes.
- If condition worsens, or if symptoms persist for more than 7 days or clear up and occur again within a few days, discontinue use of this product and consult a doctor.
- Do not apply to wounds or damaged skin. Do not bandage tightly.

Keep out of reach of children.

- Use only as directed
- Do not use if pregnant or breastfeeding
- If swallowed, get medical help or contact a Poison Control center right away.

DOSAGE AND ADMINISTRATION

Directions: Adults and children 12 years of age or older: Rub this soothing cream on the affected area not more than 3 to 4 times daily. Children under the age of 12: Do not use, consult a doctor.

Other Information: Store under normal storage conditions. Store away from children.

INACTIVE INGREDIENT

Inactive Ingredients: Water/Aqua, Cetyl Alcohol, Glycol Stearate, MSM (methylsulfonylmethane), Glycerin,

Stearyl Alcohol, Glucosamine Sulfate, Polyacrylamide (and) C13-14 Isoparaffin (and) Laureth-7, Tocopherol (Vitamin E) Acetate, Oil of Wintergreen (Methyl Salicylate), Grape Seed Oil, Sea Cucumber (Stichopus Horrens) Extract, Urea, Phenoxyethanol (and) Caprylyl Glycol (and) Sorbic Acid, Polysorbate-20, Eucalyptus Globulus Leaf Oil, Thymol, Aloe Barbadensis Leaf Juice, Chondroitin Sulfate, Magnesium Chloride

Professionl Therapy MuscleCare Maximum Strength Pain Relieving Ointment by Dr. Chris Oswald

Full product label.